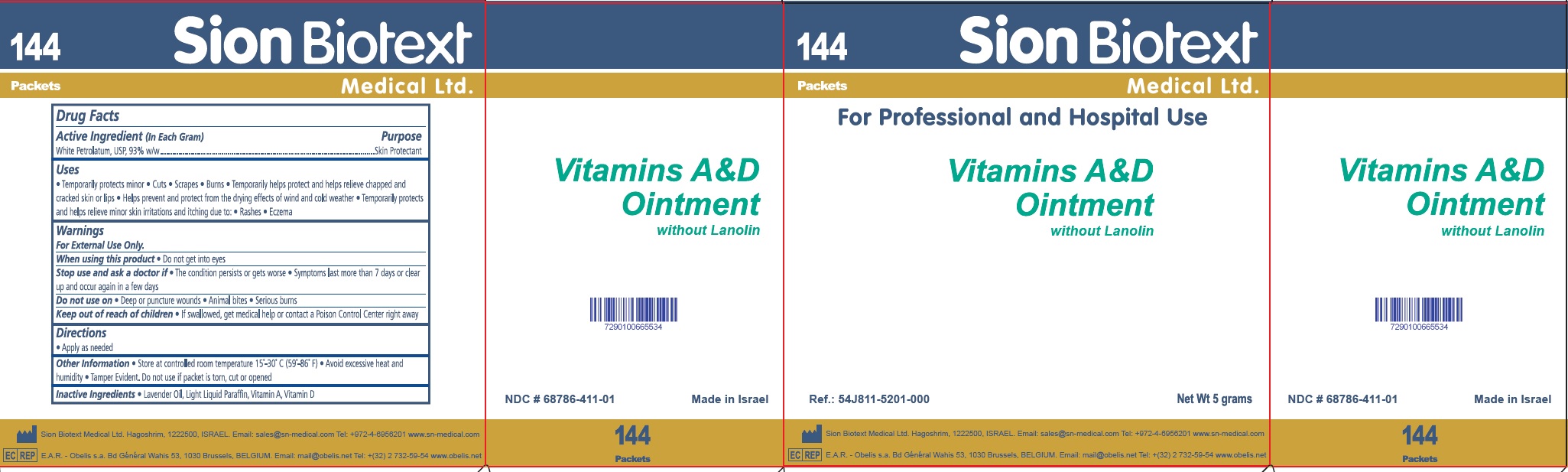 DRUG LABEL: Vitamins A and D without Lanolin
NDC: 68786-411 | Form: OINTMENT
Manufacturer: Sion Biotext Medical Ltd
Category: otc | Type: HUMAN OTC DRUG LABEL
Date: 20221212

ACTIVE INGREDIENTS: PETROLATUM 93 g/100 g
INACTIVE INGREDIENTS: LAVENDER OIL; LIGHT MINERAL OIL; VITAMIN A; VITAMIN D

Drug Facts

Active Ingredient(in Each Gram)

White Petrolatum, USP, 93% w/w

Purpose

Skin Protectant

Uses

- Temporarily protects minor
- Cuts
- Scrapes
- Burns
- Temporarily helps protect and helps relieve chapped and cracked skin or lips
- Helps prevent and protect from drying effects of wind and cold weather
- Temporarily protects and helps relieve minor skin irritation and itching due to:
- Rashes
- Eczema

Warnings

For External Use Only.

When using this product

Do not get into eyes

Stop use and ask a doctor if

- The condition persists or gets worse
- Symptoms last more than 7 days or clear up and occur again in a few days

Do not use on

- Deep or puncture wounds
- Animal bites
- Serious burns

Keep out of reach of children

- If swallowed, get medical help or contact a Poison Control Center right away

Directions

- Apply as needed

Other Information

- Store at controlled room temperature 15-30 C (59-86 F)
- Avoid excessive heat and humidity
- Tamper evident
- Do not use if packet is torn, cut or opened

Inactive Ingredients

- Lavender Oil, Light Liquid Paraffin, Vitamin A, Vitamin D

Principal Display Panel

NDC 68786-411-01

Made In Israel

144 Packets

SionBiotext Medical Ltd.

For Professional and Hospital Use

Vitamin A and D

Ointment

without Lanolin

Ref.: 54J811-5201-000

Net Wt 5 gram